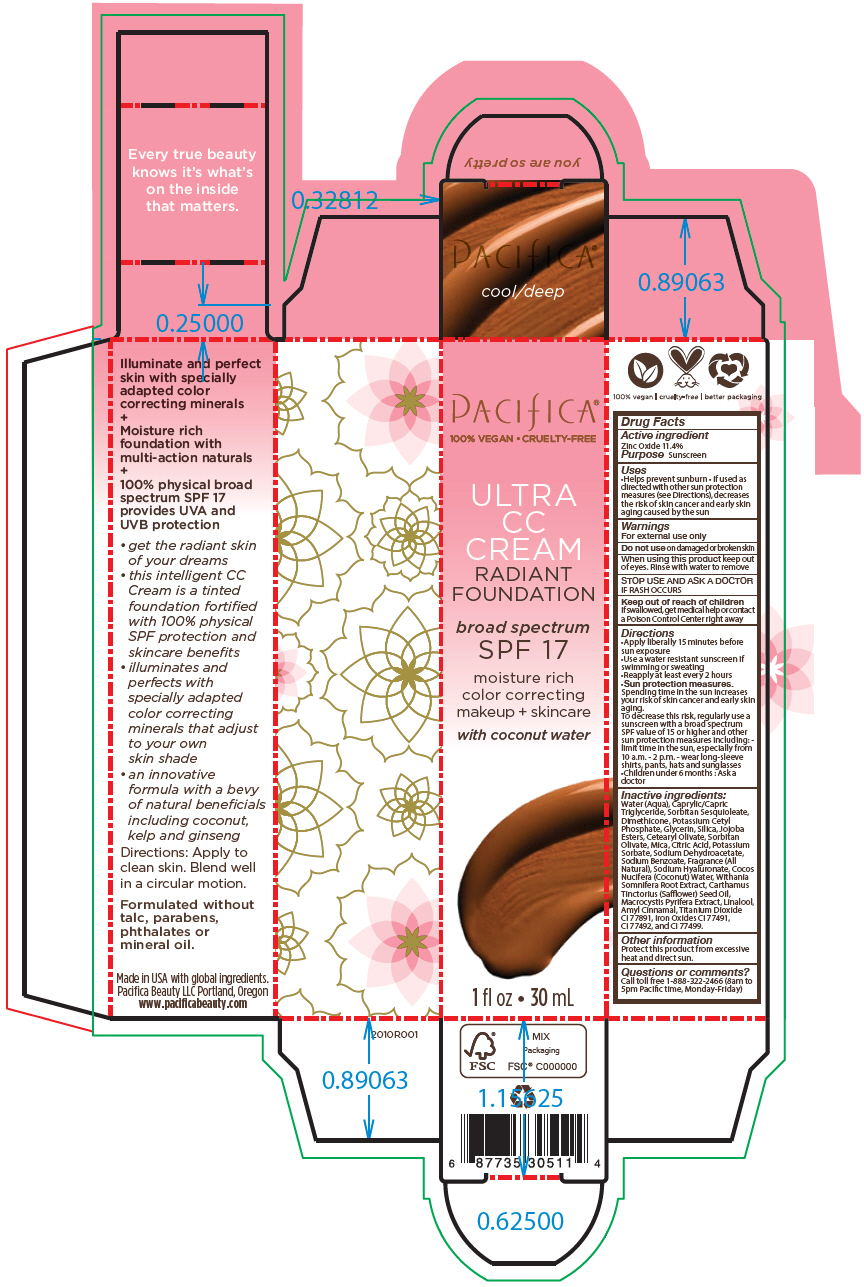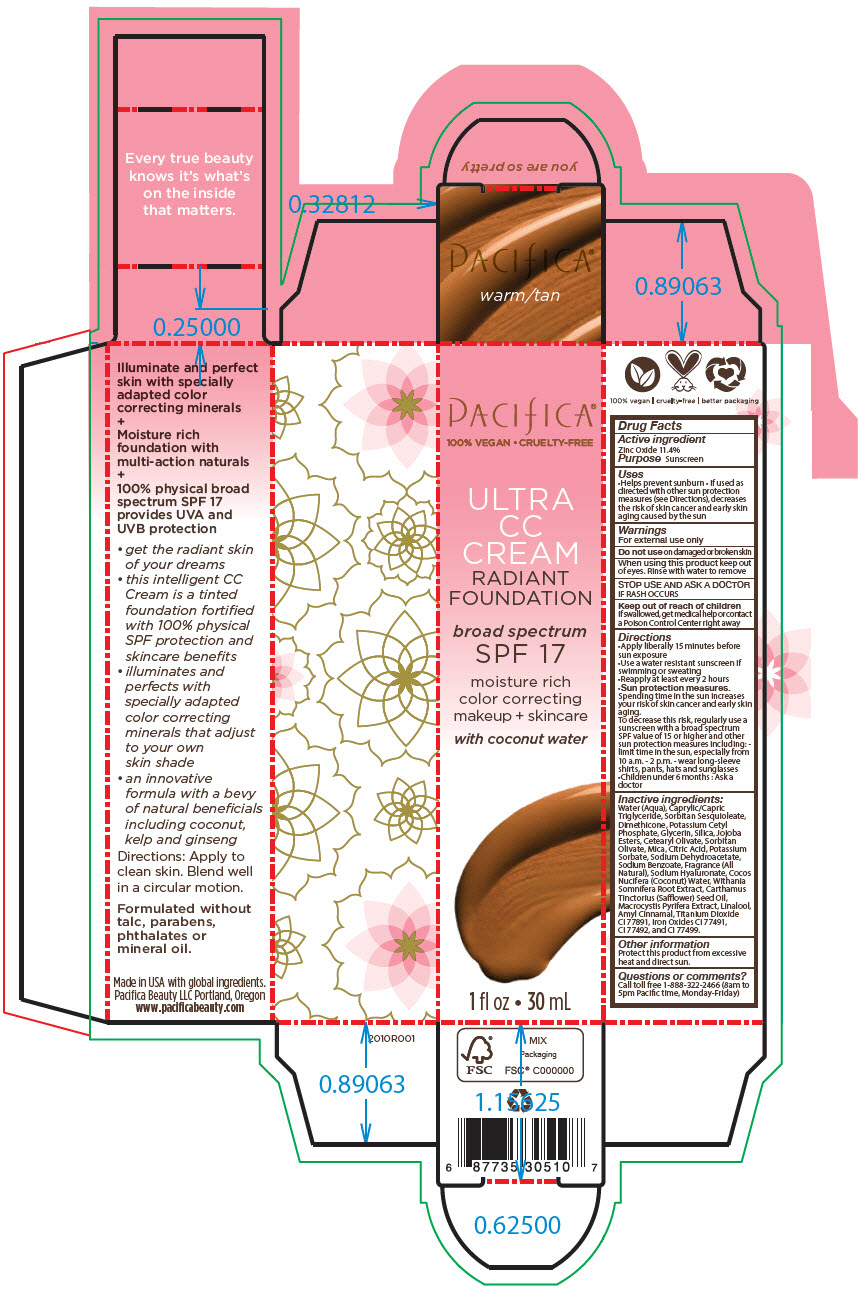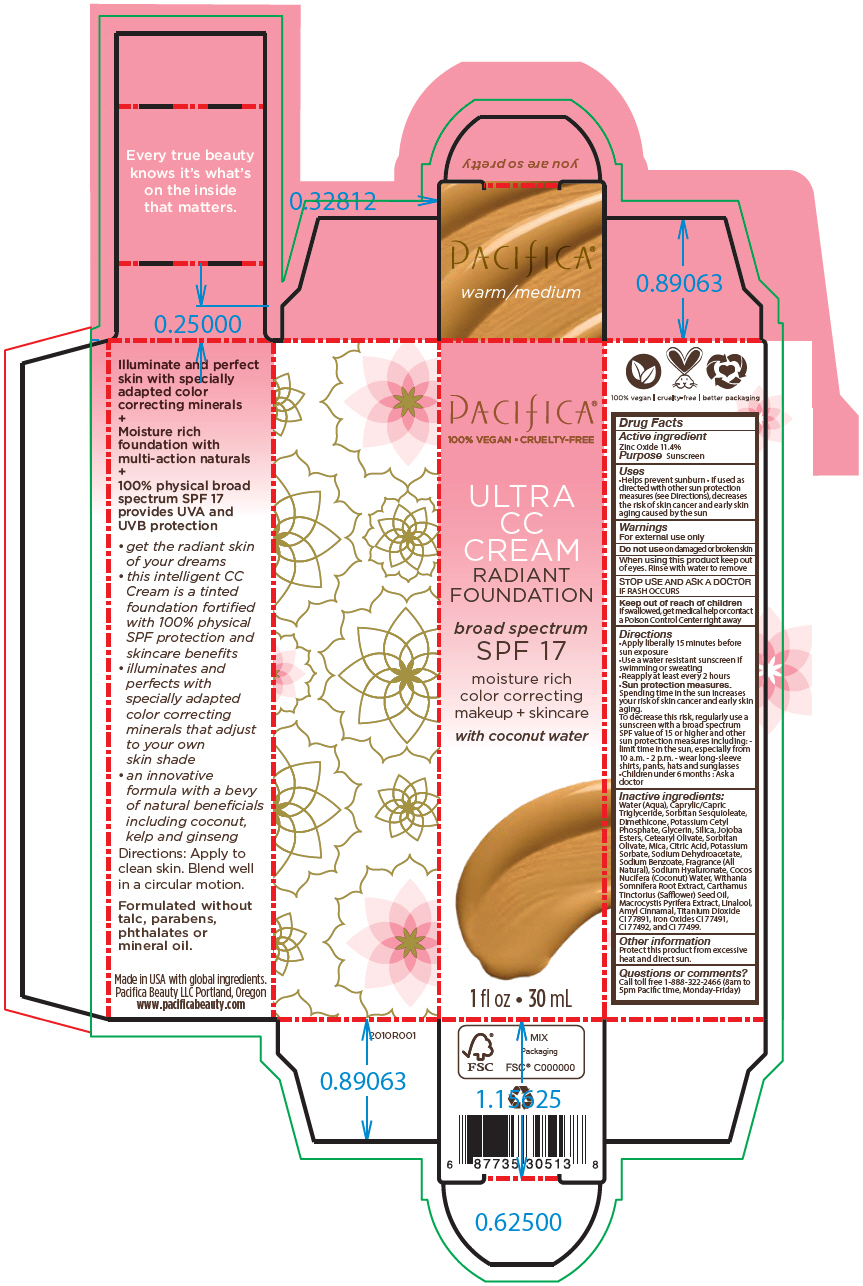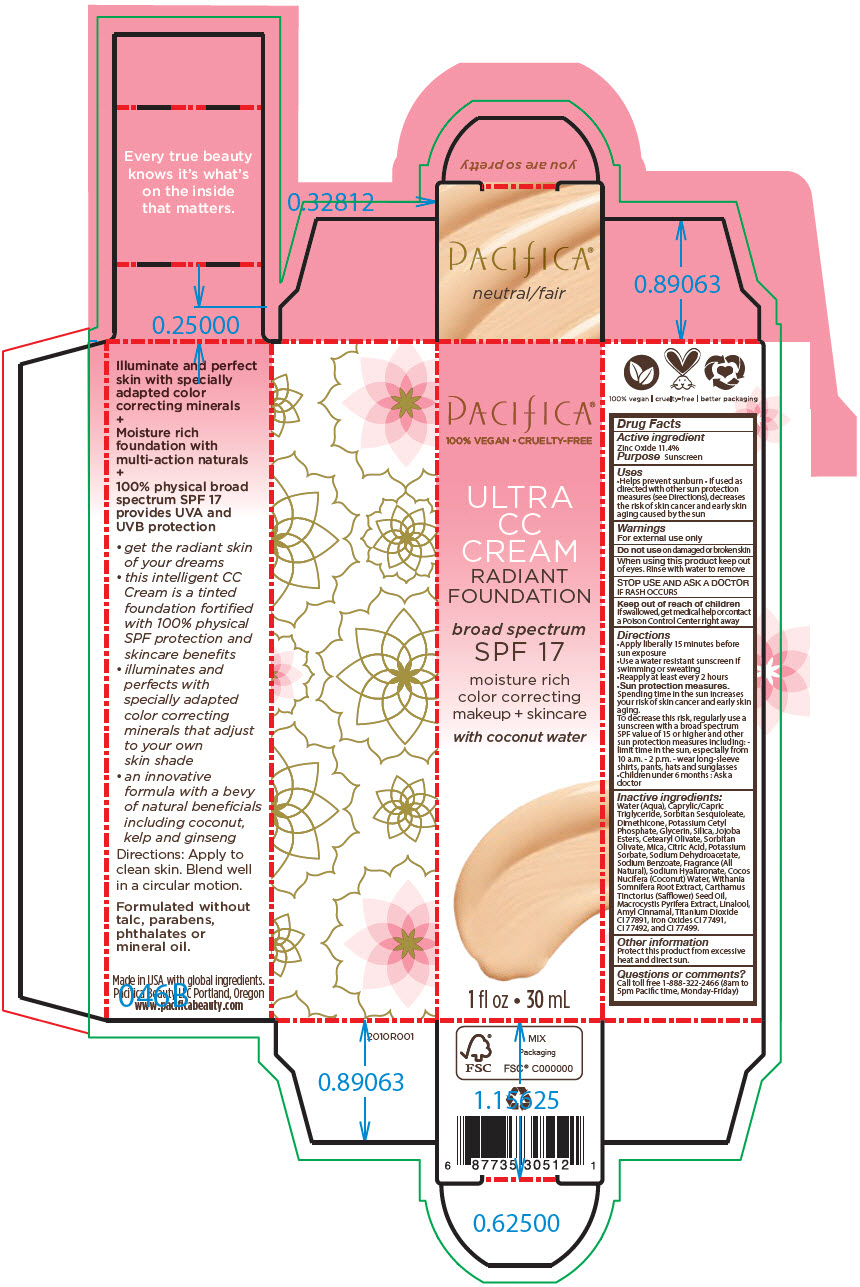 DRUG LABEL: PACIFICA ULTRA CC RADIANT FOUNDATION broad spectrum SPF 17 

NDC: 61197-201 | Form: CREAM
Manufacturer: Pacifica Beauty LLC.
Category: otc | Type: HUMAN OTC DRUG LABEL
Date: 20220411

ACTIVE INGREDIENTS: ZINC OXIDE 114 mg/1 mL
INACTIVE INGREDIENTS: WATER; MEDIUM-CHAIN TRIGLYCERIDES; SORBITAN SESQUIOLEATE; DIMETHICONE; POTASSIUM CETYL PHOSPHATE; GLYCERIN; SILICON DIOXIDE; CETEARYL OLIVATE; SORBITAN OLIVATE; MICA; CITRIC ACID MONOHYDRATE; POTASSIUM SORBATE; SODIUM DEHYDROACETATE; SODIUM BENZOATE; HYALURONATE SODIUM; COCONUT WATER; WITHANIA SOMNIFERA ROOT; SAFFLOWER OIL; MACROCYSTIS PYRIFERA; LINALOOL, (+/-)-; .ALPHA.-AMYLCINNAMALDEHYDE; TITANIUM DIOXIDE; FERRIC OXIDE RED; FERRIC OXIDE YELLOW; FERROSOFERRIC OXIDE

PACIFICA® ULTRA CC RADIANT FOUNDATION broad spectrum SPF 17

Drug Facts

Active ingredient

Zinc Oxide 11.4%

Purpose

Sunscreen

Uses

- Helps prevent sunburn
- If used as directed with other sun protection measures (see Directions), decreases the risk of skin cancer and early skin aging caused by the sun

Warnings

For external use only

Do not use on damaged or broken skin

When using this product keep out of eyes. Rinse with water to remove

STOP USE AND ASK A DOCTOR IF RASH OCCURS

Keep out of reach of children

If swallowed, get medical help or contact a Poison Control Center right away

Directions

- Apply liberally 15 minutes before sun exposure
- Use a water resistant sunscreen if swimming or sweating
- Reapply at least every 2 hours
- Sun protection measures.
  Spending time in the sun increases your risk of skin cancer and early skin aging.
  To decrease this risk, regularly use a sunscreen with a broad spectrum SPF value of 15 or higher and other sun protection measures including:
  - limit time in the sun, especially from 10 a.m. - 2 p.m.
  - wear long-sleeve shirts, pants, hats and sunglasses
- Children under 6 months : Ask a doctor

Inactive ingredients

Water (Aqua), Caprylic/Capric Triglyceride, Sorbitan Sesquioleate, Dimethicone, Potassium Cetyl Phosphate, Glycerin, Silica, Jojoba Esters, Cetearyl Olivate, Sorbitan Olivate, Mica, Citric Acid, Potassium Sorbate, Sodium Dehydroacetate, Sodium Benzoate, Fragrance (All Natural), Sodium Hyaluronate, Cocos Nucifera (Coconut) Water, Withania Somnifera Root Extract, Carthamus Tinctorius (Safflower) Seed Oil, Macrocystis Pyrifera Extract, Linalool, Amyl Cinnamal, Titanium Dioxide CI 77891, Iron Oxides CI 77491, CI 77492, and CI 77499.

Other information

Protect this product from excessive heat and direct sun.

Questions or comments?

Call toll free 1-888-322-2466 (8am to 5pm Pacific time, Monday-Friday)

PRINCIPAL DISPLAY PANEL - 30 mL Bottle Box - cool/deep

PACIFICA®
100% VEGAN • CRUELTY-FREE

ULTRA
CC
CREAM
RADIANT
FOUNDATION

broad spectrum
SPF 17

moisture rich
color correcting
makeup + skincare

with coconut water

1 fl oz • 30 mL

PRINCIPAL DISPLAY PANEL - 30 mL Bottle Box - warm/tan

PACIFICA®
100% VEGAN • CRUELTY-FREE

ULTRA
CC
CREAM
RADIANT
FOUNDATION

broad spectrum
SPF 17

moisture rich
color correcting
makeup + skincare

with coconut water

1 fl oz • 30 mL

PRINCIPAL DISPLAY PANEL - 30 mL Bottle Box - warm/medium

PACIFICA®
100% VEGAN • CRUELTY-FREE

ULTRA
CC
CREAM
RADIANT
FOUNDATION

broad spectrum
SPF 17

moisture rich
color correcting
makeup + skincare

with coconut water

1 fl oz • 30 mL

PRINCIPAL DISPLAY PANEL - 30 mL Bottle Box - neutral/fair

PACIFICA®
100% VEGAN • CRUELTY-FREE

ULTRA
CC
CREAM
RADIANT
FOUNDATION

broad spectrum
SPF 17

moisture rich
color correcting
makeup + skincare

with coconut water

1 fl oz • 30 mL